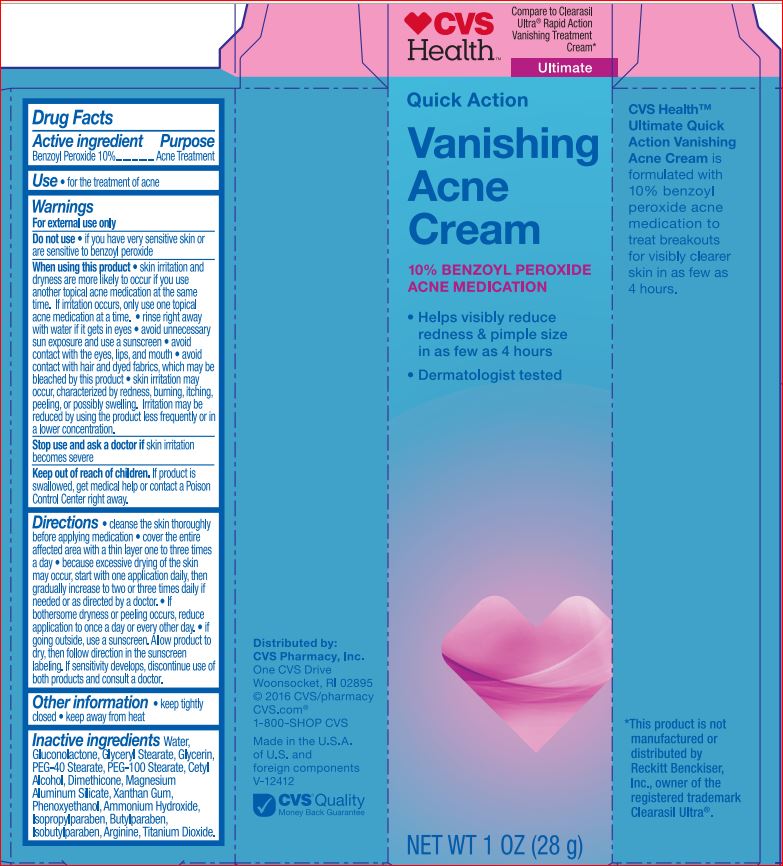 DRUG LABEL: Vanishing Acne
NDC: 69842-048 | Form: CREAM
Manufacturer: CVS
Category: otc | Type: HUMAN OTC DRUG LABEL
Date: 20171206

ACTIVE INGREDIENTS: BENZOYL PEROXIDE 10 g/100 g
INACTIVE INGREDIENTS: WATER; GLUCONOLACTONE; GLYCERYL MONOSTEARATE; PEG-100 STEARATE; GLYCERIN; PEG-40 STEARATE; CETYL ALCOHOL; DIMETHICONE; MAGNESIUM ALUMINUM SILICATE; XANTHAN GUM; PHENOXYETHANOL; AMMONIA; ISOPROPYLPARABEN; BUTYLPARABEN; ISOBUTYLPARABEN; ARGININE; TITANIUM DIOXIDE

Active ingredient

Benzoyl Peroxide 10%

Purpose

Acne Treatment

Uses

- for the treatment of acne

Warnings

For external use only

Do not use

- if you have very sensitive skin or are sensitive to benzoyl peroxide

When using this product

- skin irritation and dryness is more likely to occur if you use another topical acne medication at the same time. If irritation occurs, only use one topical acne medication at a time.
- rinse right away with water if it gets in eyes
- avoid unnecessary sun exposure and use a sunscreen
- avoid contact with the eyes, lips, and mouth.
- avoid contact with hair and dyed fabrics, which may be bleached by this product
- skin irritation may occur, characterized by redness, burning, itching, peeling, or possibly swelling. Irritation may be reduced by using the product less frequently or in a lower concentration

Stop use adn ask a doctor if

skin irritation becomes severe

Keep out of reach of children.

If product is swallowed, get medical help or contact a Poison Control Center right away.

Directions

- cleanse the skin thoroughly before applying medication
- cover the entire affected area with a thin layer one to three times a day
- because excessive drying og the skin may occur, start with one application daily, then gradually increase to two or three times daily if needed or as directed by a doctor. If bothersome dryness or peeling occurs, reduce application to once a day or every other day.
- if going outside, use a sunscreen. Allow product to dry, then follow direction in the sunscreen labeling. If sensitivity develops, discontinue use of both products and consult a doctor.

Other information

- keep tightly closed
- keep away from heat

Inactive ingredients

Water, Gluconolactone, Glyceryl Stearate, PEG-100 Stearate, Glycerin, PEG-40 Stearate, Cetyl Alcohol, Dimethicone, Magnesium Aluminum Silicate, Xanthan Gum, Phenoxyethanol, Ammonium Hydroxide, Isopropylparabem, Butylparaben, Isobutylparaben, Arginine, Titanium Dioxide.